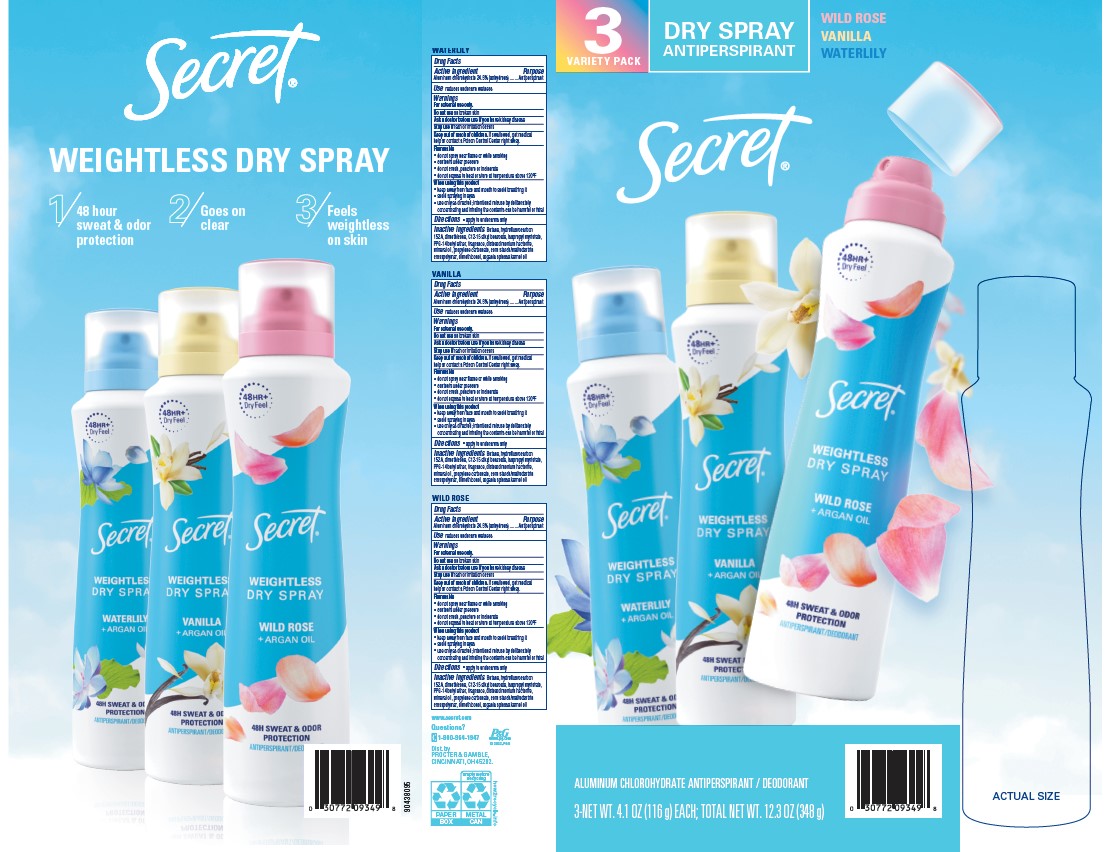 DRUG LABEL: Secret Weightless Dry Variety Pack
NDC: 84126-118 | Form: KIT | Route: TOPICAL
Manufacturer: The Procter & Gamble Manufacturing Company
Category: otc | Type: HUMAN OTC DRUG LABEL
Date: 20250513

ACTIVE INGREDIENTS: ALUMINUM CHLOROHYDRATE 24.5 g/100 g; ALUMINUM CHLOROHYDRATE 24.5 g/100 g; ALUMINUM CHLOROHYDRATE 24.5 g/100 g
INACTIVE INGREDIENTS: DIMETHICONE; MINERAL OIL; BUTANE; PPG-14 BUTYL ETHER; DIMETHICONOL (100000 CST); ISOPROPYL MYRISTATE; ARGANIA SPINOSA KERNEL OIL; C12-15 ALKYL BENZOATE; HYDROFLUOROCARBON 152A; DISTEARDIMONIUM HECTORITE; PROPYLENE CARBONATE; DIMETHICONE; MINERAL OIL; BUTANE; PPG-14 BUTYL ETHER; DIMETHICONOL (100000 CST); ISOPROPYL MYRISTATE; ARGANIA SPINOSA KERNEL OIL; C12-15 ALKYL BENZOATE; HYDROFLUOROCARBON 152A; DISTEARDIMONIUM HECTORITE; PROPYLENE CARBONATE; DIMETHICONE; MINERAL OIL; BUTANE; PPG-14 BUTYL ETHER; DIMETHICONOL (100000 CST); ISOPROPYL MYRISTATE; ARGANIA SPINOSA KERNEL OIL; C12-15 ALKYL BENZOATE; HYDROFLUOROCARBON 152A; DISTEARDIMONIUM HECTORITE; PROPYLENE CARBONATE

Secret Weightless Dry Spray Variety Pack

WATERLILY

Drug Facts

Active ingredient

Aluminum Chlorohydrate 24.5% (anhydrous)

Purpose

Antiperspirant

Uses

reduces underarm wetness

Warnings

For external use only.

Do not use on broken skin

Ask a doctor before use if you have kidney disease

Stop use if rash or irritation occurs

KEEP OUT OF REACH OF CHILDREN

Keep this and all drugs out of reach of children.

If swallowed, get medical help or contact a Poison Control Center right away.

Flammable

• do not spray near flame or while smoking
• contents under pressure
• do not crush, puncture or incinerate
• do not expose to heat or store at temperature above 120ºF

When using this product

• keep away from face and mouth to avoid breathing it
• avoid spraying in eyes
• use only as directed; intentional misuse by deliberately
concentrating and inhaling the contents can be harmful or fatal

Directions

- apply to underarms only

Inactive ingredients

Butane, hydrofluorocarbon 152A, dimethicone, C12-15 alkyl benzoate, isopropyl myristate, PPG-14 butyl ether, fragrance, disteardimonium hectorite, mineral oil, propylene carbonate, corn starch/maltodextrin crosspolymer, dimethiconol, argania spinosa kernel oil

VANILLA

Drug Facts

Active ingredient

Aluminum Chlorohydrate 24.5% (anhydrous)

Purpose

Antiperspirant

Use

reduces underarm wetness

WARNINGS

For external use only.

Do not use on broken skin

Ask a doctor before use if you have kidney disease

Stop use if rash or irritation occurs

Keep out of reach of children. If swallowed, get medical help or contact a Poison Control Center right away.

Flammable

• do not spray near flame or while smoking
• contents under pressure
• do not crush, puncture or incinerate
• do not expose to heat or store at temperature above 120ºF

WHEN USING

• keep away from face and mouth to avoid breathing it
• avoid spraying in eyes
• use only as directed; intentional misuse by deliberately
concentrating and inhaling the contents can be harmful or fatal

Directions

apply to underarms only

Inactive ingredients

Butane, hydrofluorocarbon 152A, dimethicone, C12-15 alkyl benzoate, isopropyl myristate, PPG-14 butyl ether, fragrance, disteardimonium hectorite, mineral oil, propylene carbonate, corn starch/maltodextrin crosspolymer, dimethiconol, argania spinosa kernel oil

WILD ROSE

Drug Facts

ACTIVE INGREDIENT

Aluminum chlorohydrate 24.5% (anhydrous)

PURPOSE

Antiperspirant

Use

reduces underarm wetness

WARNINGS

For external use only.

Do not use on broken skin

Ask a doctor before use if you have kidney disease

Stop use if rash or irritation occurs

Keep out of reach of children.

If swallowed, get medical help or contact a Poison Control Center right away.

Flammable

• do not spray near flame or while smoking
• contents under pressure
• do not crush, puncture or incinerate
• do not expose to heat or store at temperature above 120ºF

When using this product

• keep away from face and mouth to avoid breathing it
• avoid spraying in eyes
• use only as directed; intentional misuse by deliberately concentrating and inhaling the contents can be harmful or fatal

Directions

• apply to underarms only

Inactive ingredients

Butane, hydrofluorocarbon 152A, dimethicone, C12-15 alkyl benzoate, isopropyl myristate, PPG-14 butyl ether, fragrance, disteardimonium hectorite, mineral oil, propylene carbonate, corn starch/maltodextrin crosspolymer, dimethiconol, argania spinosa kernel oil

Questions (or comments)?

1-800-964-1947

Dist. by PROCTER & GAMBLE,
CINCINNATI, OH 45202

PRINCIPAL DISPLAY PANEL - Kit

SECRET

3 VARIETY PACK

DRY SPRAY

ANTIPERSPIRANT

WILD ROSE

VANILLA

WATERLILY

ALUMINUM CHLOROHYDRATE ANTIPERSPIRANT/DEODORANT

3-NEW WT. 4.1 OZ (116 g) EACH; TOTAL NET WT. 12.3 OZ (348 g)